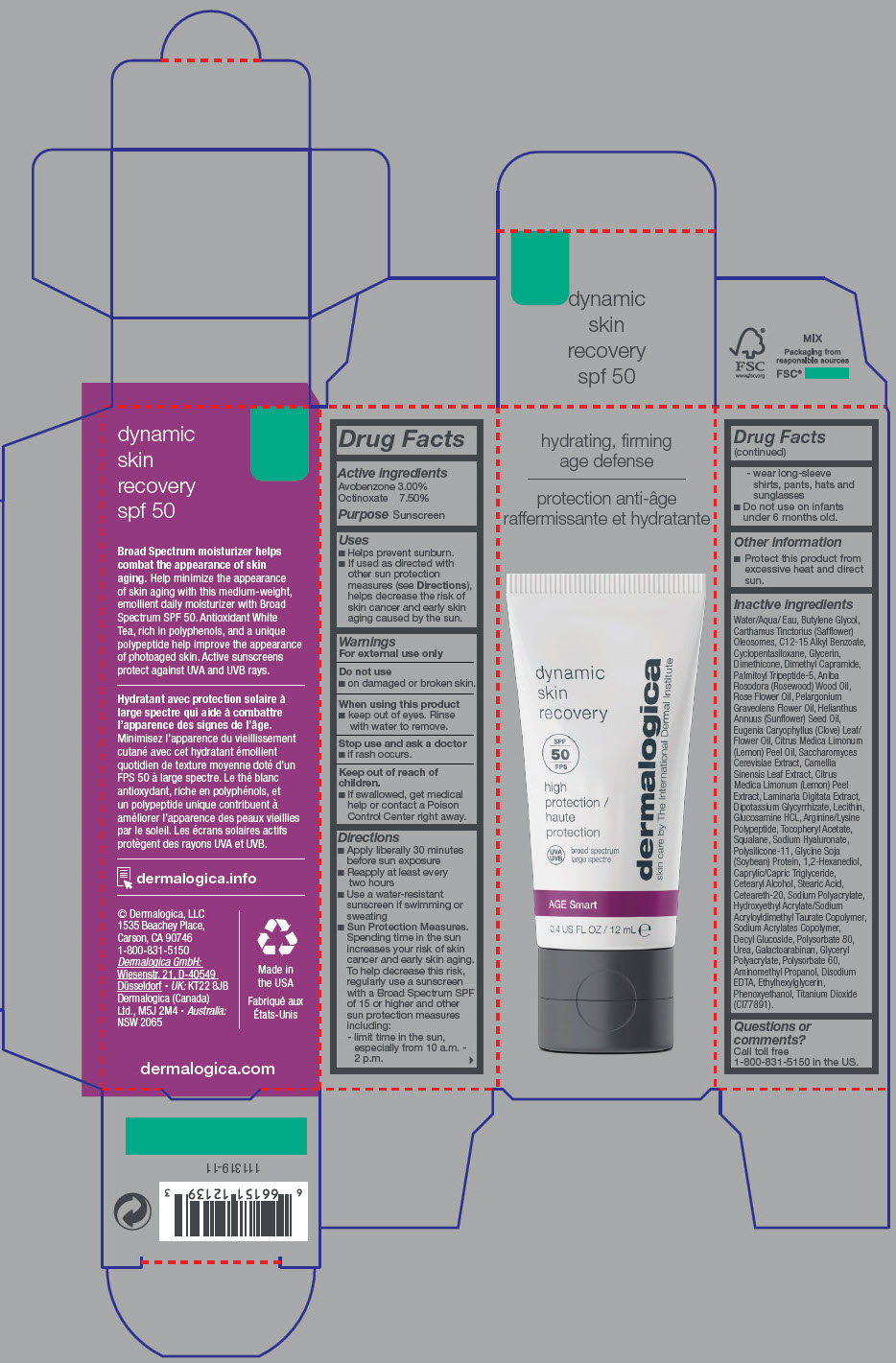 DRUG LABEL: Dynamic Skin Recovery 
NDC: 68479-318 | Form: LOTION
Manufacturer: Dermalogica, Inc.
Category: otc | Type: HUMAN OTC DRUG LABEL
Date: 20220714

ACTIVE INGREDIENTS: Avobenzone 30 mg/1 mL; Octinoxate 75 mg/1 mL
INACTIVE INGREDIENTS: Water; Butylene Glycol; CARTHAMUS TINCTORIUS SEED OLEOSOMES; ALKYL (C12-15) BENZOATE; CYCLOMETHICONE 5; Glycerin; GREEN TEA LEAF; DIMETHICONE; Dimethyl Capramide; PHENOXYETHANOL; Polysorbate 80; HYDROXYETHYL ACRYLATE/SODIUM ACRYLOYLDIMETHYL TAURATE COPOLYMER (100000 MPA.S AT 1.5%); CETOSTEARYL ALCOHOL; Squalane; DIMETHICONE/VINYL DIMETHICONE CROSSPOLYMER (SOFT PARTICLE); LECITHIN, SOYBEAN; Titanium Dioxide; Galactoarabinan; SUNFLOWER OIL; Stearic Acid; EDETATE DISODIUM ANHYDROUS; Gluconic Acid; GLYCYRRHIZINATE DIPOTASSIUM; Ethylhexylglycerin; Polysorbate 60; AMINOMETHYLPROPANOL; ROSEWOOD OIL; POLYOXYL 20 CETOSTEARYL ETHER; 1,2-Hexanediol; 1-DEHYDRO-7.ALPHA.-METHYLTESTOSTERONE; Sodium Benzoate; CLOVE OIL; Urea; GLUCOSAMINE HYDROCHLORIDE; LEMON OIL, COLD PRESSED; Pelargonium Graveolens Flower Oil; LAMINARIA DIGITATA; SACCHAROMYCES CEREVISIAE; ROSA X ALBA FLOWER OIL; Palmitoyl Tripeptide-5; Tocopherol; Decyl Glucoside; BUTYLATED HYDROXYTOLUENE; MEDIUM-CHAIN TRIGLYCERIDES; LEMON PEEL; HYALURONATE SODIUM; Cupressus Sempervirens Leaf Oil; PALMAROSA OIL; Methylparaben; Cymbopogon Schoenanthus Oil; EUCALYPTUS OIL; ROSA X DAMASCENA FLOWER OIL; SOY PROTEIN; LINALOOL, (+/-)-; Eugenol; LIMONENE, (+)-; .BETA.-CITRONELLOL, (R)-; Geraniol

Dynamic Skin Recovery
SPF 50

Drug Facts

Active ingredients

Avobenzone (3.0%)
Octinoxate (7.5%)

Purpose

Sunscreen

Uses

- Helps prevent sunburn.
- If used as directed with other sun protection measures (see Directions), helps decrease the risk of skin cancer and early skin aging caused by the sun.

Warnings

For external use only

Do not use on damaged or broken skin.

When using this product keep out of eyes. Rinse with water to remove.

Stop use and ask a doctor if rash occurs.

Keep out of reach of children. If swallowed, get medical help or contact a Poison Control Center right away.

Directions

- Apply liberally 30 minutes before sun exposure
- Reapply at least every two hours
- Use a water-resistant sunscreen if swimming or sweating
- Sun Protection Measures. Spending time in the sun increases your risk of skin cancer and early skin aging. To help decrease this risk, regularly use a sunscreen with a Broad Spectrum SPF of 15 or higher and other sun protection measures including:
  1. limit time in the sun, especially from 10 a.m. – 2 p.m.
  2. wear long-sleeve shirts, pants, hats and sunglasses
- Do not use on infants under 6 months old.

Other information

- Protect this product from excessive heat and direct sun.

Inactive ingredients

Water/Aqua/ Eau, Butylene Glycol, Carthamus Tinctorius (Safflower) Oleosomes, C12-15 Alkyl Benzoate, Cyclopentasiloxane, Glycerin, Dimethicone, Dimethyl Capramide, Palmitoyl Tripeptide-5, Aniba Rosodora (Rosewood) Wood Oil, Rose Flower Oil, Pelargonium Graveolens Flower Oil, Helianthus Annuus (Sunflower) Seed Oil, Eugenia Caryophyllus (Clove) Leaf/Flower Oil, Citrus Medica Limonum (Lemon) Peel Oil, Saccharomyces Cerevisiae Extract, Camellia Sinensis Leaf Extract, Citrus Medica Limonum (Lemon) Peel Extract, Laminaria Digitata Extract, Dipotassium Glycyrrhizate, Lecithin, Glucosamine HCL, Arginine/Lysine Polypeptide, Tocopheryl Acetate, Squalane, Sodium Hyaluronate, Polysilicone-11, Glycine Soja (Soybean) Protein, 1,2-Hexanediol, Caprylic/Capric Triglyceride, Cetearyl Alcohol, Stearic Acid, Ceteareth-20, Sodium Polyacrylate, Hydroxyethyl Acrylate/Sodium Acryloyldimethyl Taurate Copolymer, Sodium Acrylates Copolymer, Decyl Glucoside, Polysorbate 80, Urea, Galactoarabinan, Glyceryl Polyacrylate, Polysorbate 60, Aminomethyl Propanol, Disodium EDTA, Ethylhexylglycerin, Phenoxyethanol, Titanium Dioxide (CI77891).

Questions or comments

Call toll free 1-800-831-5150 in the US.

PRINCIPAL DISPLAY PANEL - 12 mL Bottle Carton

hydrating, firming
age defense

dynamic
skin
recovery

SPF
50

high
protection

UVA
UVB
broad spectrum

dermalogica
skin care by The International Dermal Institute

AGE Smart

0.4 US FL OZ / 12 mL e